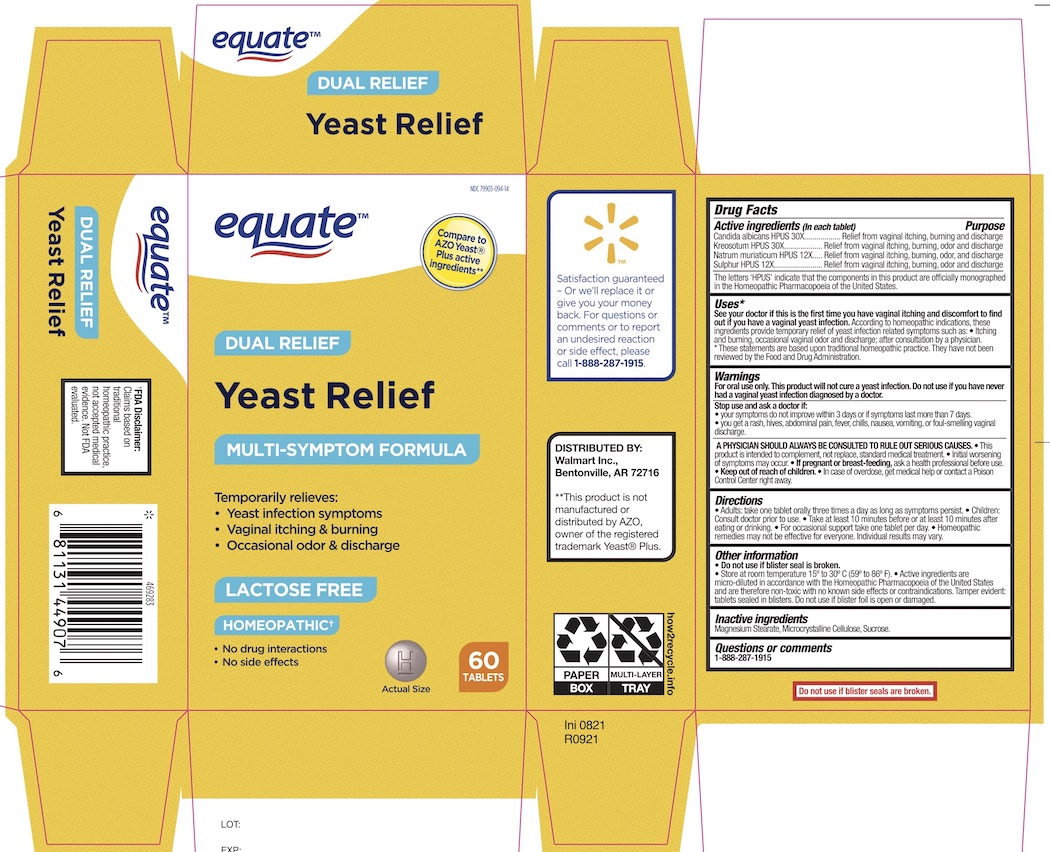 DRUG LABEL: Equate Yeast Relief
NDC: 79903-094 | Form: TABLET
Manufacturer: WAL-MART STORES INC
Category: homeopathic | Type: HUMAN OTC DRUG LABEL
Date: 20251217

ACTIVE INGREDIENTS: CANDIDA ALBICANS 30 [hp_X]/1 1; WOOD CREOSOTE 30 [hp_X]/1 1; SODIUM CHLORIDE 12 [hp_X]/1 1; SULFUR 12 [hp_X]/1 1
INACTIVE INGREDIENTS: SUCROSE; MAGNESIUM STEARATE; CELLULOSE, MICROCRYSTALLINE

Equate Yeast Relief

Active Ingredients

Candida albicans 30X

Kreosotum 30X

Natrium muriaticum 12X

Sulphur 12X

Purpose

Candida albicans 30X - Relief from vaginal itching, burning and discharge

Candida albicans 30X - Relief from vaginal itching, burning, odor and discharge

Kreosotum 30X - Relief from vaginal itching, burning, odor and discharge

Natrium muriaticum 12X - Relief from vaginal itching, burning, odor and discharge

Sulphur 12X - Relief from vaginal itching, burning, odor and discharge

Uses

See your doctor if this is the first time you have vaginal itching and discomfort to find out if you have a vaginal yeast infection. According to homeopathic indications, these ingredients provide temporary relief of yeast infection related symprtoms such as:

- itching and burning, occasional vaginal odor and discharge, after consultation by a physician.

*These statements are based upon traditional homeopathic practice. They have not been reviewed by the Food and Drug Administration.

Warnings

For oral use only. This product will not cure a yeast infection. Do not use if you have never had a vaginal yeast infection diagnosed by a doctor.

Stop use and contact your physician if

- your symptoms do not improve within 3 days or if symptoms last more than 7 days.
- you get a rash, hives, abdominal pain, fever, chills, nausea, vomiting, or foul-smelling vaginal discharge.

Ask Doctor

A PHYSICIAN SHOULD ALWAYS BE CONSULTED TO RULE OUT SERIOUS CONDITIONS.

- This product is intended to complement, not replace, standard medical treatment.
- Initial worsening of symptoms may occur.

Pregnancy warning

If pregnant or breastfeeding, ask a health professional before use.

Keep out of reach of children. If swallowed, get medical help or contact a Poison Control Center right away.

Directions

Adults: take one tablet orally three times a day as long as symptoms persist. Children: consult a doctor prior to use.

- Take at least 10 minutes before or at least 10 minutes after eating or drinking.
- For occasional support take one tablet per day.
- Homeopathic remedies may not be effective for everyone. Individual results may vary.

Other Information

- Do not use if blister seal is broken.
- Store at 15° to 30°C (59° to 86° F).
- Active ingredients are micro-diluted in accordance with the Hemeopathic Pharmacopoeia of the United States and are therefore non-toxic with no known side effects or contraindications. Tamper evident: tablets sealed in blisters. Do not use if blister is open or damaged.

Inactive Ingredients

Magnesium stearate, and Microcrystalline Cellulose, Sucrose.

Questions or comments

Quesitons? 1-888-287-1915